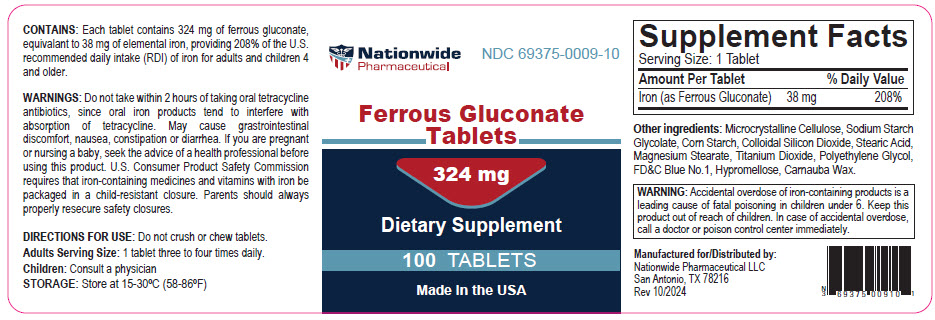 DRUG LABEL: FERROUS GLUCONATE
NDC: 69375-009 | Form: TABLET
Manufacturer: Nationwide Pharmaceutical LLC
Category: other | Type: DIETARY SUPPLEMENT
Date: 20241011

ACTIVE INGREDIENTS: FERROUS GLUCONATE 38 mg/1 1
INACTIVE INGREDIENTS: MICROCRYSTALLINE CELLULOSE; SILICON DIOXIDE; STEARIC ACID; MAGNESIUM STEARATE; TITANIUM DIOXIDE; SODIUM STARCH GLYCOLATE Type B Potato; STARCH, CORN; POLYETHYLENE GLYCOL, UNSPECIFIED; FD&C BLUE NO. 1; HYPROMELLOSE, UNSPECIFIED; CARNAUBA WAX

Ferrous Gluconate Tablets

CONTAINS

Each tablet contains 324 mg of ferrous gluconate, equivalant to 38 mg of elemental iron, providing 208% of the U.S. recommended daily intake (RDI) of iron for adults and children 4 and older.

WARNINGS

Do not take within 2 hours of taking oral tetracycline antibiotics, since oral iron products tend to interfere with absorption of tetracycline. May cause grastrointestinal discomfort, nausea, constipation or diarrhea. If you are pregnant or nursing a baby, seek the advice of a health professional before using this product. U.S. Consumer Product Safety Commission requires that iron-containing medicines and vitamins with iron be packaged in a child-resistant closure. Parents should always properly resecure safety closures.

DIRECTIONS FOR USE

Do not crush or chew tablets.

Adults Serving Size: 1 tablet three to four times daily.
Children: Consult a physician

STORAGE

Store at 15-30°C (58-86°F)

STATEMENT OF IDENTITY

Supplement Facts
Serving Size: 1 Tablet
Amount Per Tablet |  | % Daily Value
Iron (as Ferrous Gluconate) | 38 mg | 208%

Other ingredients: Microcrystalline Cellulose, Sodium Starch Glycolate, Corn Starch, Colloidal Silicon Dioxide, Stearic Acid, Magnesium Stearate, Titanium Dioxide, Polyethylene Glycol, FD&C Blue No.1, Hypromellose, Carnauba Wax.

SAFE HANDLING WARNING

WARNING: Accidental overdose of iron-containing products is a leading cause of fatal poisoning in children under 6. Keep this product out of reach of children. In case of accidental overdose, call a doctor or poison control center immediately.

HEALTH CLAIM

Manufactured for/Distributed by:
Nationwide Pharmaceutical LLC
San Antonio, TX 78216
Rev 10/2024

PRINCIPAL DISPLAY PANEL - 324 mg Tablet Bottle Label

Nationwide
Pharmaceutical

NDC 69375-0009-10

Ferrous Gluconate
Tablets

324 mg

Dietary Supplement

100 TABLETS

Made in the USA